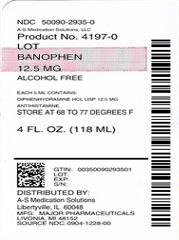 DRUG LABEL: banophen
NDC: 50090-2935 | Form: LIQUID
Manufacturer: A-S Medication Solutions
Category: otc | Type: HUMAN OTC DRUG LABEL
Date: 20190201

ACTIVE INGREDIENTS: DIPHENHYDRAMINE HYDROCHLORIDE 12.5 mg/5 mL
INACTIVE INGREDIENTS: ANHYDROUS CITRIC ACID; D&C RED NO. 33; FD&C RED NO. 40; WATER; SODIUM BENZOATE; SACCHARIN SODIUM; SODIUM CITRATE, UNSPECIFIED FORM; SORBITOL; GLYCERIN; POLYSORBATE 20; CHERRY

Banophen™ Allergy

Drug Facts

Active ingredient (in each 5 mL)

Diphenhydramine HCl USP 12.5 mg

Purpose

Antihistamine

Uses

temporarily relieves these symptoms of hay fever or other upper respiratory allergies

- runny nose
- sneezing
- itchy, watery eyes
- itching of the nose or throat

Warnings

Do not use

- to make a child sleepy
- with any other product containing diphenhydramine, including one applied topically.

Ask a doctor before use if you have

- glaucoma
- a sodium restricted diet
- trouble urinating due to an enlarged prostate gland
- a breathing problem such as emphysema or chronic bronchitis

Ask a doctor or pharmacist before use if you are taking sedatives or tranquilizers.

When using this product

- marked drowsiness may occur
- avoid alcoholic drinks
- alcohol, sedatives, and tranquilizers may increase drowsiness
- use caution when driving a motor vehicle or operating machinery
- excitability may occur, especially in children

PREGNANCY OR BREAST FEEDING

If pregnant or breast-feeding, ask a health professional before use.

KEEP OUT OF REACH OF CHILDREN

Keep out of the reach of children. In case of overdose, get medical help or contact a Poison Control Center right away (1-800-222-1222).

Directions

- take every 4 to 6 hours
- do not take more than 6 doses in 24 hours
- use only with enclosed dosing cup. Do not use with any other device
- find right dose on chart below
- mL = milliliter

adults and children 12 years and over | 10-20mL (25 mg to 50 mg)
children 6 to under 12 years | 5-10mL (12.5 mg to 25 mg)
children 2 to 5 years of age | do not use unless directed by a doctor
children under 2 years of age | do not use

Other information

- each (5 mL) contains: sodium 7 mg
- TAMPER-EVIDENT: Do not use this product if inner foil seal over the mouth of the bottle is cut, torn, broken or missing
- store at room temperature 20°-25°C (68°-77°F)

Inactive ingredients

artificial cherry flavor, citric acid, D&C Red #33, FD&C Red #40, glycerin, polysorbate 20, purified water, saccharin sodium, sodium benzoate, sodium citrate, sorbitol solution

Questions or comments?

(800) 616-2471

Distributed by:
MAJOR® PHARMACEUTICALS
17177 N Laurel Park Drive, Suite 233
Livonia, MI 48152

HOW SUPPLIED

Product: 50090-2935

NDC: 50090-2935-0 118 mL in a BOTTLE / 1 in a CARTON